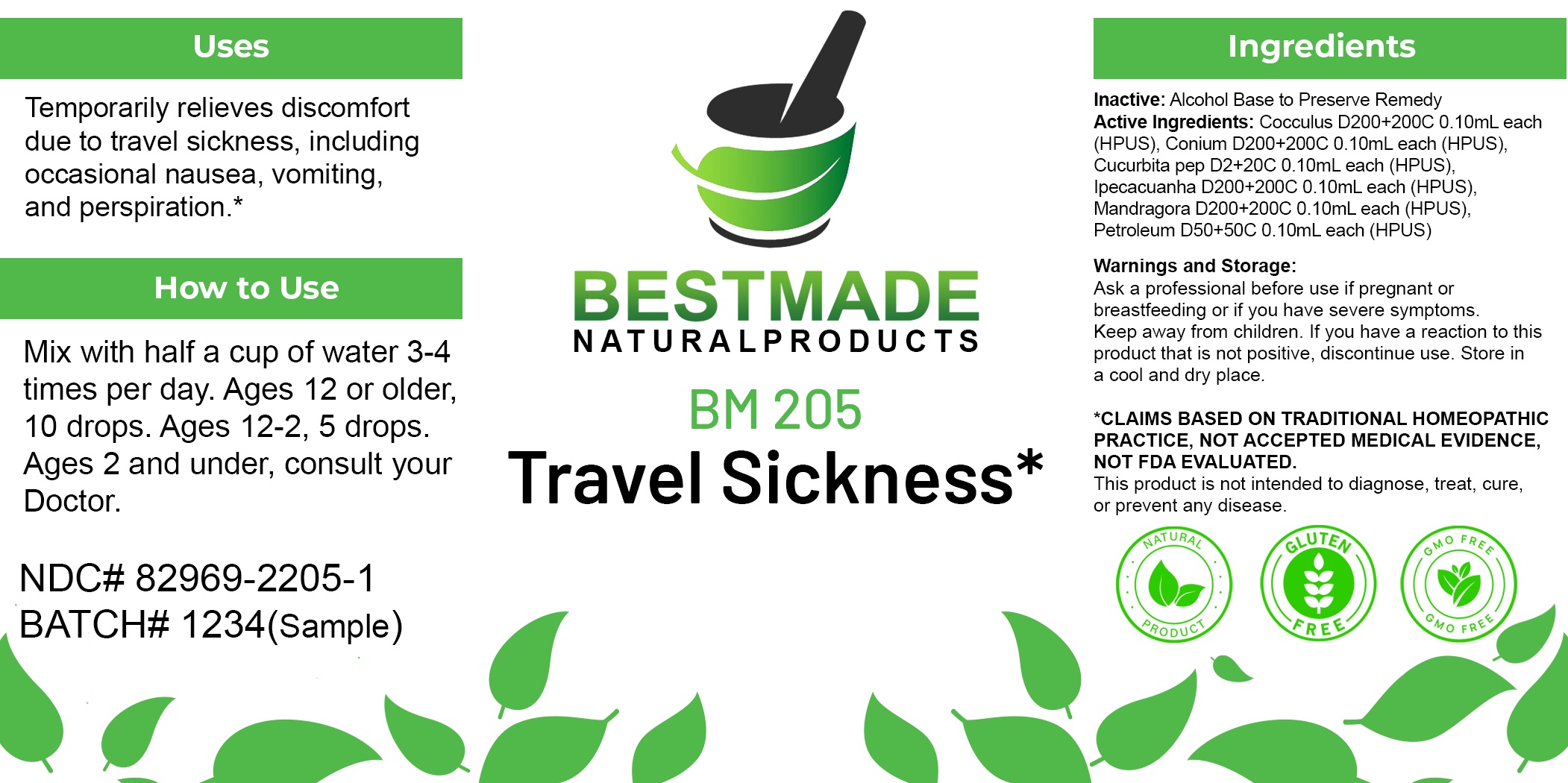 DRUG LABEL: Bestmade Natural Products BM205
NDC: 82969-2205 | Form: LIQUID
Manufacturer: Bestmade Natural Products
Category: homeopathic | Type: HUMAN OTC DRUG LABEL
Date: 20250228

ACTIVE INGREDIENTS: ANAMIRTA COCCULUS SEED 30 [hp_C]/30 [hp_C]; IPECAC 30 [hp_C]/30 [hp_C]; CONIUM MACULATUM FLOWERING TOP 30 [hp_C]/30 [hp_C]; KEROSENE 30 [hp_C]/30 [hp_C]; PUMPKIN SEED 30 [hp_C]/30 [hp_C]; MANDRAGORA OFFICINARUM ROOT 30 [hp_C]/30 [hp_C]
INACTIVE INGREDIENTS: ALCOHOL 30 [hp_C]/30 [hp_C]

BM205

DOSAGE AND ADMINISTRATION

How to Use

Mix with half a cup of water 3-4 times per day. Ages 12 or older, 10 drops. Ages 12-2, 5 drops. Ages 2 and under, consult your Doctor.

Inactive:

Alcohol Base to Preserve Product

ACTIVE INGREDIENT

Active Ingredients: Cocculus D200+200C 0.10mL each (HPUS), Conium D200+200C 0.10mL each (HPUS), Cucurbita pep D2+20C 0.10mL each (HPUS), Ipecacuanha D200+200C 0.10mL each (HPUS), Mandragora D200+200C 0.10mL each (HPUS), Petroleum D50+50C 0.10mL each (HPUS)

KEEP OUT OF REACH OF CHILDREN

Warnings and Storage:

Ask a professional before use if pregnant or breastfeeding or if you have severe symptoms.

Keep away from children. If you have a reaction to this product that is not positive, discontinue use. Store in a cool and dry place

*CLAIMS BASED ON TRADITIONAL HOMEOPATHIC PRACTICE, NOT ACCEPTED MEDICAL EVIDENCE NOT FDA EVALUATED.
This product is not intended to diagnose, treat, cure, or prevent any disease.

Warnings and Storage:

Ask a professional before use if pregnant or breastfeeding or if you have severe symptoms.

Keep away from children. If you have a reaction to this product that is not positive, discontinue use. Store in a cool and dry place

*CLAIMS BASED ON TRADITIONAL HOMEOPATHIC PRACTICE, NOT ACCEPTED MEDICAL EVIDENCE NOT FDA EVALUATED.
This product is not intended to diagnose, treat, cure, or prevent any disease.

Uses
Temporarily relieves discomfort due to travel sickness, including occasional nausea, vomiting, and perspiration.*

Uses
Temporarily relieves discomfort due to travel sickness, including occasional nausea, vomiting, and perspiration.*

Entire package label